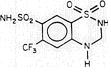 DRUG LABEL: Unknown
Manufacturer: Shire
Category: prescription | Type: Human prescription drug label
Date: 20060719

SALURON®
(Hydroflumethiazide)

Description

Saluron® (hydroflumethiazide) is a potent oral diuretic-antihypertensive agent of low toxicity. Each tablet contains 50 mg of hydroflumethiazide.

Saluron® is 2H-1,2,4-Benzothiadiazine-7-sulfonamide, 3,4-dihydro-6-(trifluoromethyl)-, 1,1-dioxide. Hydroflumethiazide is very slightly soluble in water, soluble in methanol and freely soluble in acetone. Inactive ingredients: microcrystalline cellulose, lactose, magnesium stearate, colloidal silicon dioxide, and sodium starch glycolate. It has the following structural formula:

Clinical Pharmacology

Hydroflumethiazide is incompletely but fairly rapidly absorbed from the gastrointestinal tract. It appears to have a biphasic biological half-life with an estimated alpha-phase of about 2 hours and an estimated beta-phase of about 17 hours; it has a metabolite with a longer half-life, which is extensively bound to the red blood cells. Hydroflumethiazide is excreted in the urine; its metabolite has also been detected in the urine.

The mechanism of action results in an interference with the renal tubular mechanism of electrolyte reabsorption. At maximal therapeutic dosage, all thiazides are approximately equal in their diuretic potency. The mechanism whereby thiazides function in the control of hypertension is unknown.

Indications and Usage

Saluron® is indicated as adjunctive therapy in edema associated with congestive heart failure, hepatic cirrhosis and corticosteroid and estrogen therapy.

Saluron® has also been found useful in edema due to various forms of renal dysfunction, such as nephrotic syndrome, acute glomerulonephritis, and chronic renal failure.

Saluron® is indicated in the management of hypertension, either as the sole therapeutic agent or to enhance the effectiveness of other antihypertensive drugs in the more severe forms of hypertension.

Usage In Pregnancy

The routine use of diuretics in an otherwise healthy woman is inappropriate and exposes mother and fetus to unnecessary risk. Diuretics do not prevent development of toxemia of pregnancy, and there is no satisfactory evidence that they are useful in the treatment of developed toxemia.

Edema during pregnancy may arise from pathological causes or from the physiologic and mechanical consequences of pregnancy. Thiazides are indicated in pregnancy when edema is due to pathologic causes, just as they are in the absence of pregnancy (however, see Warnings below). Dependent edema in pregnancy, resulting from restriction of venous return by the expanded uterus, is properly treated through elevation of the lower extremities and use of support hose. Use of diuretics to lower intravascular volume in this case is illogical and unnecessary. There is hypervolemia during normal pregnancy which is harmful to neither the fetus nor the mother (in the absence of cardiovascular disease), but which is associated with edema, including generalized edema, in the majority of pregnant women. If this edema produces discomfort, increased recumbency will often provide relief. In rare instances, this edema may cause extreme discomfort which is not relieved by rest. In these cases, a short course of diuretics may provide relief and may be appropriate.

Contraindications

Saluron® is contraindicated in patients with anuria or hypersensitivity to this or other sulfonamide-derived drugs.

Warnings

Saluron® should be used with caution in severe renal disease. In patients with renal disease, thiazide may precipitate azotemia. Cumulative effects of the drug may develop in patients with impaired renal function.

Thiazides should be used with caution in patients with impaired hepatic function or progressive liver disease, since minor alterations of fluid and electrolyte balance may precipitate hepatic coma.

Thiazides may be additive or potentiative of the action of other antihypertensive drugs. Potentiation occurs with ganglionic or peripheral adrenergic blocking drugs.

Sensitivity reactions may occur in patients with a history of allergy or bronchial asthma.

The possibility of exacerbation or activation of systemic lupus erythematosus has been reported.

Precautions

General

All patients receiving thiazide therapy should be observed for clinical signs of fluid or electrolyte imbalance, namely, hyponatremia. hypochloremic alkalosis, and hypokalemia. Serum and urine electrolyte determinations are particularly important when the patient is vomiting excessively or receiving parenteral fluids. Medication such as digitalis may also influence serum electrolytes. Warning signs, irrespective of cause, are: dryness of mouth, thirst, weakness, lethargy, drowsiness, restlessness, muscle pains or cramps, muscular fatigue, hypotension, oliguria, tachycardia, and gastrointestinal disturbances such as nausea and vomiting.

Hypokalemia may develop with thiazides as with any other potent diuretic, especially with brisk diuresis. when severe cirrhosis is present, or during concomitant use of corticosteroids, including ACTH.

Interference with adequate oral electrolyte intake will also contribute to hypokalemia. Digitalis therapy may exaggerate the metabolic effects of hypokalemia, especially with respect to myocardial activity.

Any chloride deficit is generally mild and usually does not require specific treatment, except under extraordinary circumstances (as in liver disease or renal disease). Dilutional hyponatremia may occur in edematous patients in hot weather. Appropriate therapy is water restriction, rather than administration of salt, except in rare instances when the hyponatremia is life-threatening. In actual salt depletion, appropriate replacement is the therapy of choice.

Hyperuricemia may occur or frank gout may be precipitated in certain patients receiving thiazide therapy.

Insulin requirements in diabetic patients may be increased, decreased, or unchanged. Latent diabetes mellitus may become manifested during thiazide administration.

Thiazide drugs may increase the responsiveness to tubocurarine.

The antihypertensive effects of the drug may be enhanced in the postsympathectomy patient.

Thiazides may decrease arterial responsiveness to norepinephrine. This diminution is not sufficient to preclude effectiveness of the pressor agent for therapeutic use.

If progressive renal impairment becomes evident, as indicated by rising nonprotein nitrogen or blood urea nitrogen, a careful reappraisal of therapy is necessary with consideration given to withholding or discontinuing diuretic therapy.

Thiazides may decrease serum PBI levels without signs of thyroid disturbance.

Lithium generally should not be given with diuretics, because they reduce its renal clearance and increase the risk of lithium toxicity. Read circulars for lithium preparations before use of such concomitant therapy with Saluron®.

Information for Patients

This medicine may cause a loss of potassium from your body. To help prevent this, your doctor may want you to:

- take another medicine or
- eat or drink foods having high potassium content (such as orange or other citrus fruit juices), or
- take a potassium supplement

It is very important to follow these directions. Also, it is important not to change your diet on your own. This is more important if you are already on a special diet (as for diabetes), or if you are taking a potassium supplement or a medicine to reduce potassium loss. Extra potassium may not be necessary and, in some cases, could be harmful.

Check with your doctor if you become sick and have severe or continuing vomiting or diarrhea. These problems may cause you to lose additional water and potassium.

Caution: Diabetics-Thiazide diuretics may raise blood sugar levels. While you are using this medicine, be especially careful in testing for sugar in your urine. If you have any questions about this, check with your doctor.

A few people who take this medicine may become more sensitive to sunlight than they are normally. When you begin to take this medicine, avoid too much sun or use of a sunlamp until you see how you react, especially if you tend to burn easily. If you have a severe reaction, check with your doctor.

For patients taking this medicine for high blood pressure:

•Do not take other medicines unless they have been discussed with your doctor. This especially includes over-the-counter (nonprescription) medicines for appetite control, asthma, colds, cough, hay fever, or sinus.

Laboratory Tests

Periodic determination of serum electrolytes to detect possible electrolyte imbalance should be performed at appropriate intervals.

Drug Interactions

Anticoagulants (oral): effects may be decreased when used concurrently with thiazide diuretics; dosage adjustments may be necessary.

Antigout medications: thiazide diuretics may raise the level of blood uric acid; dosage adjustment of antigout medications may be necessary to control hyperuricemia and gout.

Other antihypertensive medications, especially diazoxide; pre-anesthetic and anesthetic agents used in surgery; skeletal muscle relaxants, nondepolarizing, used in surgery: effects may be potentiated when used concurrently with thiazide diuretics; dosage adjustments may be necessary.

Amphotericin B or Corticosteroids, including Corticotropin (ACTH): concurrent use with thiazide diuretics may intensify electrolyte imbalance, particularly hypokalemia.

Cardiac glycosides: concurrent use with thiazide diuretics may enhance the possibility of digitalis toxicity associated with hypokalemia.

Colestipol: may inhibit gastrointestinal absorption of the thiazide diuretics; administration 1 hour before or 4 hours after colestipol is recommended.

Hypoglycemics: thiazide diuretics may raise blood glucose levels. For adult-onset diabetics, dosage adjustment of hypoglycemic medications may be necessary during and after thiazide diuretic therapy; insulin requirements may be increased, decreased, or unchanged.

Lithium salts: concurrent use with thiazide diuretics is not recommended, as they may provoke lithium toxicity because of reduced renal clearance.

Methenamine: effectiveness may be decreased when used concurrently with thiazide diuretics, because of alkalinization of the urine.

Diagnostic Interference

With expected physiologic effects.

Blood and urine glucose levels: usually only in patients with a predisposition to glucose intolerance.

Serum bilirubin levels: displacement from albumin binding.

Serum calcium levels: thiazide diuretics should be discontinued before parathyroid function tests are carried out.

Serum uric acid levels: may be increased.

Serum magnesium, potassium, and sodium levels: may be decreased, serum magnesium levels may increase in uremic patients.

Serum protein-bound iodine (PBI) levels: may be decreased.

Carcinogenesis, Mutagenesis, Impairment of Fertility

No long-term studies in animals have been performed to evaluate carcinogenic or mutagenic potential or impairment of fertility.

Pregnancy

Pregnancy Category D. See "WARNINGS"Section.

Teratogenic Effects

Saluron® can cause fetal harm when administered to a pregnant woman. The hazards include fetal or neonatal jaundice, thrombocytopenia, and possibly other adverse reactions which have occurred in adults. If this drug is used during pregnancy, or if the patient becomes pregnant while taking this drug, the patient should be apprised of the potential hazard to the fetus.

Nonteratogenic Effects

Fetal or neonatal jaundice, thrombocytopenia, and possibly other adverse reactions which have occurred in adults.

Nursing Mothers

Thiazides appear in breast milk. If use of the drug is deemed essential, the patient may consider stopping nursing.

Pediatric Use

Safety and effectiveness in children have not been established.

Adverse Reactions

The following adverse reactions have been observed, but there has not been enough systematic collection of data to support an estimate of their frequency.

Gastrointestinal system reactions: anorexia, gastric irritation, nausea, vomiting, cramping, diarrhea, constipation, jaundice (intrahepatic cholestatic jaundice), pancreatitis.

Central nervous system reactions: dizziness, vertigo, parathesias, headache, xanthopsia.

Hematologic reactions: leukopenia, agranulocytosis, thrombocytopenia, aplastic anemia.

Dermatologic-Hypersensitivity reactions: purpura, photosensitivity, rash, urticaria, necrotizing angiitis (vasculitis) (cutaneous vasculitis).

Cardiovascular reaction: orthostatic hypotension may occur and may be aggravated by alcohol, barbiturates, or narcotics.

Other: hyperglycemia, glycosuria, hyperuricemia, muscle spasm, weakness, restlessness.

Whenever adverse reactions are moderate or severe, thiazide dosage should be reduced or therapy withdrawn.

Overdosage

Signs and Symptoms

Diuresis, lethargy progressing to coma, with minimal cardiorespiratory depression and with or without significant serum electrolyte changes or dehydration; GI irritation; hypermotility; transient elevation of BUN level.

Treatment

Empty stomach by gastric lavage, taking care to avoid aspiration. Monitor serum electrolyte levels and renal function, and institute supportive measures, as required to maintain hydration, electrolyte balance, respiration, and cardiovascular and renal function. Treat GI effects symptomatically.

Dosage and Administration

In the treatment of edema, the usual initial dose is 50 to 200 mg daily, in 1 or 2 divided doses, reduced to a dose of 25 to 50 mg on alternate days or intermittently. In the treatment of hypertension, the usual dose is 25 to 50 mg daily in 1 or 2 divided doses, either alone, or in conjunction with other antihypertensive agents. A suggested initial dose for children is 1 mg per kg of body weight daily, reduced for maintenance.

Therapy should be individualized according to patient response. This therapy should be titrated to gain maximal therapeutic response, as well as the minimal dose possible to maintain that therapeutic response.

How Supplied

Saluron® Tablets, scored, 50 mg in bottles of 100.

NDC 54092-055-01

Store from 15° to 25°C (59° to 77°F).

Keep this and all medication out of the reach of children.

CAUTION: Federal law prohibits dispensing without prescription.